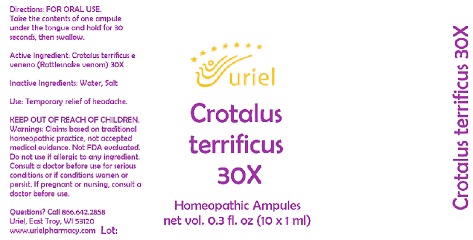 DRUG LABEL: Crotalus terrificus 30X
NDC: 48951-3249 | Form: LIQUID
Manufacturer: Uriel Pharmacy, Inc.
Category: homeopathic | Type: HUMAN OTC DRUG LABEL
Date: 20211026

ACTIVE INGREDIENTS: CROTALUS DURISSUS TERRIFICUS VENOM 30 [hp_X]/1 mL
INACTIVE INGREDIENTS: SODIUM CHLORIDE; WATER

Crotalus terrificus 30X

INDICATIONS AND USAGE

Directions: FOR ORAL USE.

DOSAGE AND ADMINISTRATION

Take the contents of one ampule under the tongue and hold for 30 seconds, then swallow.

Active Ingredient: Crotalus terrificus e veneno (Rattlesnake venom) 30X

Inactive Ingredients: Water, Salt

PURPOSE

Use: Temporary relief of headache.

KEEP OUT OF REACH OF CHILDREN.

WARNINGS

Warnings: Claims based on traditional homeopathic practice, not accepted medical evidence. Not FDA evaluated. Do not use if allergic to any ingredient. Consult a doctor before use for serious conditions or if conditions worsen or persist. If pregnant or nursing, consult a doctor before use.

Questions? Call 866.642.2858
Uriel, East Troy, WI 53120
www.urielpharmacy.com Lot#